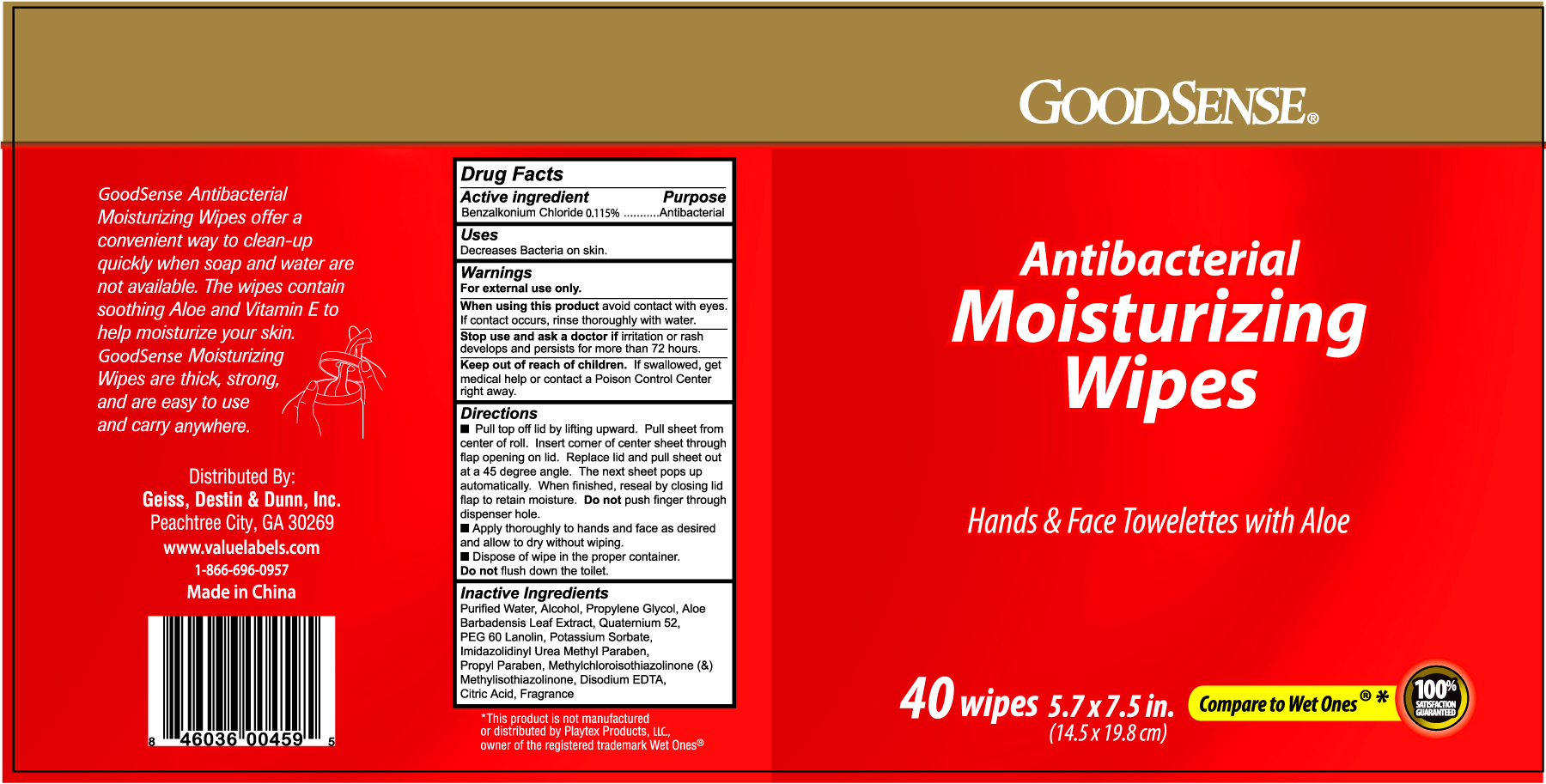 DRUG LABEL: GOODSENSE ANTIBACTERIAL MOISTURIZING
NDC: 75981-004 | Form: FILM
Manufacturer: GEISS, DESTIN AND DUNN, INC.
Category: otc | Type: HUMAN OTC DRUG LABEL
Date: 20110221

ACTIVE INGREDIENTS: BENZALKONIUM CHLORIDE 0.115 g/100 1
INACTIVE INGREDIENTS: WATER; ALCOHOL; PROPYLENE GLYCOL; ALOE VERA LEAF; POTASSIUM SORBATE; EDETATE DISODIUM; CITRIC ACID MONOHYDRATE

Drug Facts

Active ingredient Purpose

Benzalkonium Chloride 0.115% ..........................................Antibacterial

Uses

Decreases Bacteria on skin

Warnings

For external use only.

When using this product avoid contact with eyes.

If contact occurs, rinse thoroughly with water.

Stop use and ask a doctor if irritation or rash develops and persists for more than 72 hours.

Keep out of reach of children. If swallowed, get medical help or contact a Poison Control Center right away.

Directions

- Pull top off lid by lifting upward. Pull sheet from center of roll. Insert corner of center sheet through flap opening on lid. Replace lid and pull sheet out at a 45 degree angle. The next sheet pops up automatically. When finished, reseal by closing lid flap to retain moisture. Do not push finger through dispenser hole.
- Apply thoroughly to hands and face as desired and allow to dry without wiping.
- Dispose of wipe in the proper container.
- Do not flush down the toilet

Inactive Ingredients

Purified Water, Alcohol, Propylene Glycol, Aloe Barbadensis Leaf Extract, Quatemium 52, PEG 60 Lanolin, Potassium Sorbate, Imidazolidinyl Urea Methyl Paraben, Propyl Paraben, Methylchloroisothiazolinone and Methylisothiazolinone, Disodium EDTA, Citric Acid, Fragrance

DOSAGE AND ADMINISTRATION

Distributed By:

Geiss, Destin and Dunn, Inc.

Peachtree City, GA 30269

www.valuelabels.com

1-866-696-0957

Made in China

PACKAGE LABEL

Enter section text here